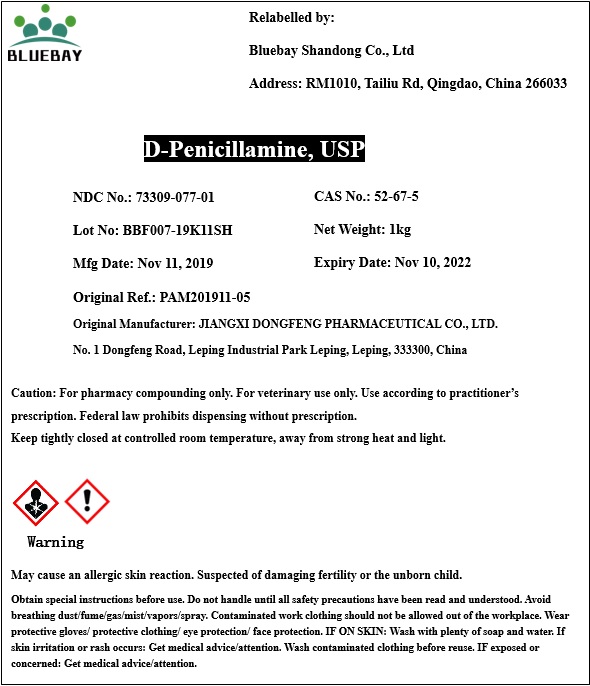 DRUG LABEL: D-Penicillamine
NDC: 73309-077 | Form: POWDER
Manufacturer: BLUEBAY SHANDONG CO.,LTD
Category: other | Type: BULK INGREDIENT
Date: 20200110

ACTIVE INGREDIENTS: PENICILLAMINE 1 kg/1 kg

D-Penicillamine